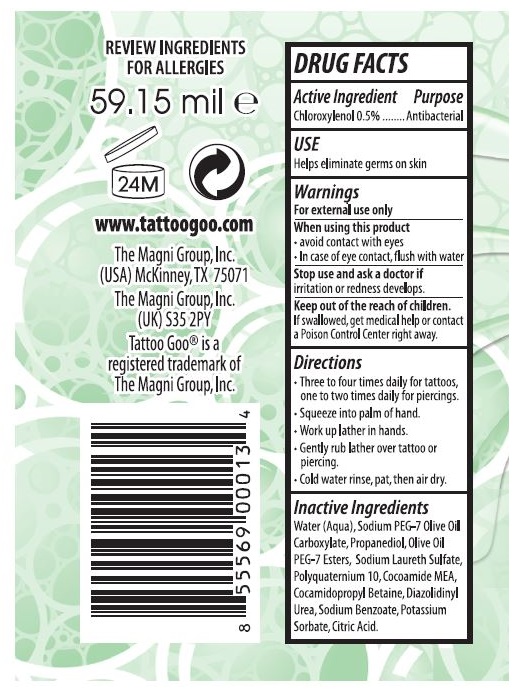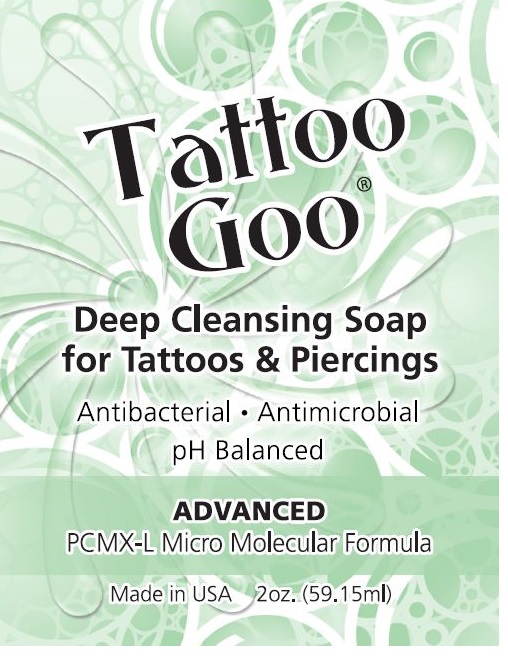 DRUG LABEL: Tattoo Goo
NDC: 43689-0056 | Form: LIQUID
Manufacturer: The Magni Group Inc
Category: otc | Type: HUMAN OTC DRUG LABEL
Date: 20200826

ACTIVE INGREDIENTS: CHLOROXYLENOL 0.5 mg/100 mL
INACTIVE INGREDIENTS: SODIUM LAURETH SULFATE; ANHYDROUS CITRIC ACID; WATER; POLYQUATERNIUM-10 (1000 MPA.S AT 2%); COCO MONOETHANOLAMIDE; COCAMIDOPROPYL BETAINE; POTASSIUM SORBATE; DIAZOLIDINYL UREA; SODIUM BENZOATE; OLIVE OIL POLYGLYCERYL-6 ESTERS; PROPANEDIOL; POLYETHYLENE GLYCOL, UNSPECIFIED

Active Ingredient: Chloroxylenol 0.5% Purpose: Antibacterial

NDC: 43689-0056-1

Purpose: Antibacterial

NDC: 43689-0056-1

Use: Helps eliminate germs on skin

NDC: 43689-0056-1

Warnings: For external use only

NDC: 43689-0056-1

When using this product: -avoid contact with eyes -In case of eye contact, flush with water

NDC: 43689-0056-1

Stop use and ask a doctor if irritation or redness develops.

NDC: 43689-0056-1

Keep out of the reach of children. If swallowed, get medical help or contact a Poison Control Center right away.

NDC: 43689-0056-1

Directions -Three to four times daily for tattoos, one to two times daily for piercings. -Squeeze into palm of hand. -Work up lather in hands. -Gently rub lather over tattoo or piercing. -Cold water rinse, pat, then air dry.

NDC: 43689-0056-1

Inactive Ingredients: Water (Aqua), Sodium PEG-7 Olive Oil Carboxylate, Propanediol, Olive Oil PEG-7 Esters, Sodium Laureth Sulfate, Polyquaternium 10, Cocoamide MEA, Cocamidopropyl Betaine, Diazolidinyl Urea, Sodium Benzoate, Potassium Sorbate, Citric Acid.

NDC:43689-0056-1

Principal Display Panel

NDC: 43689-0056-1